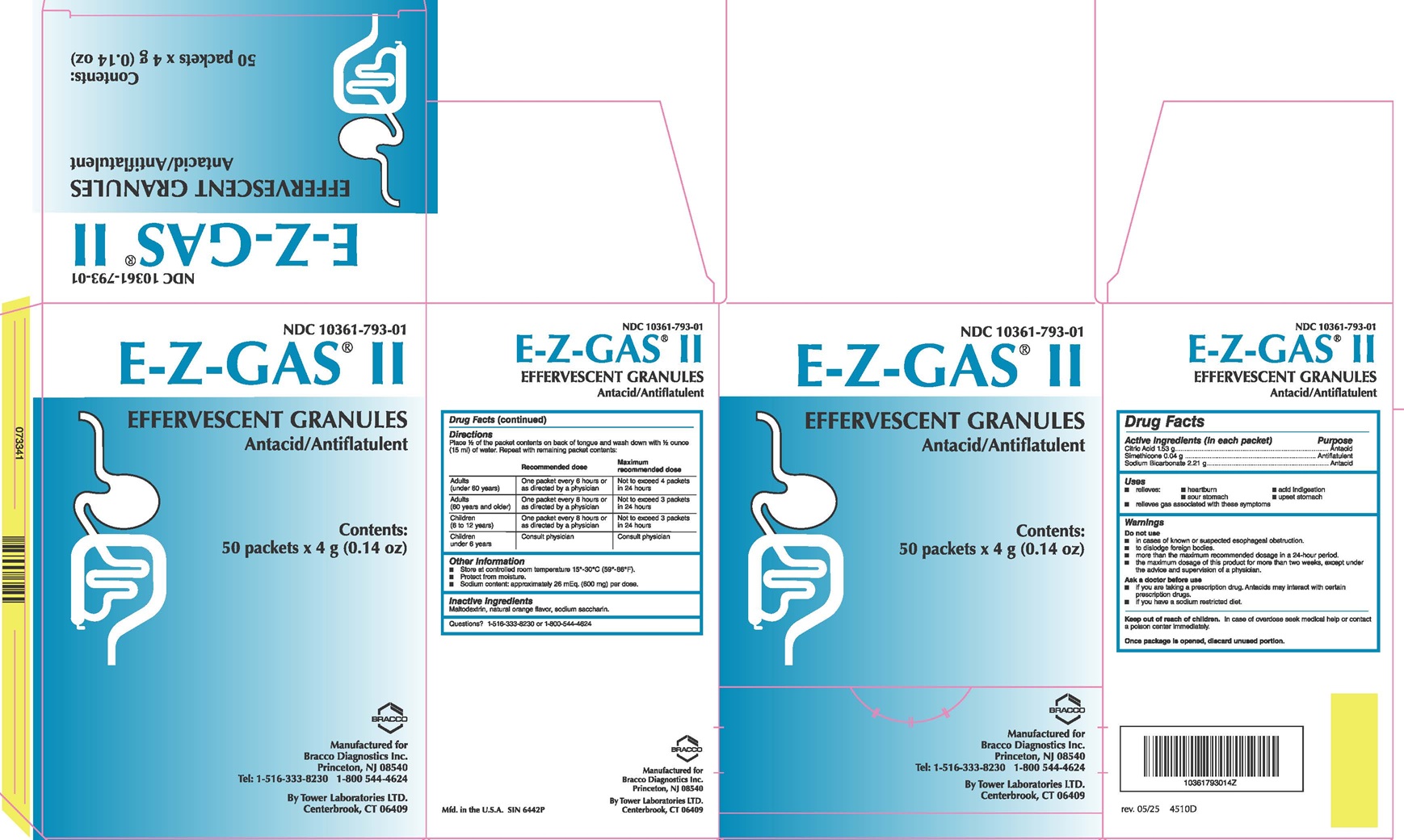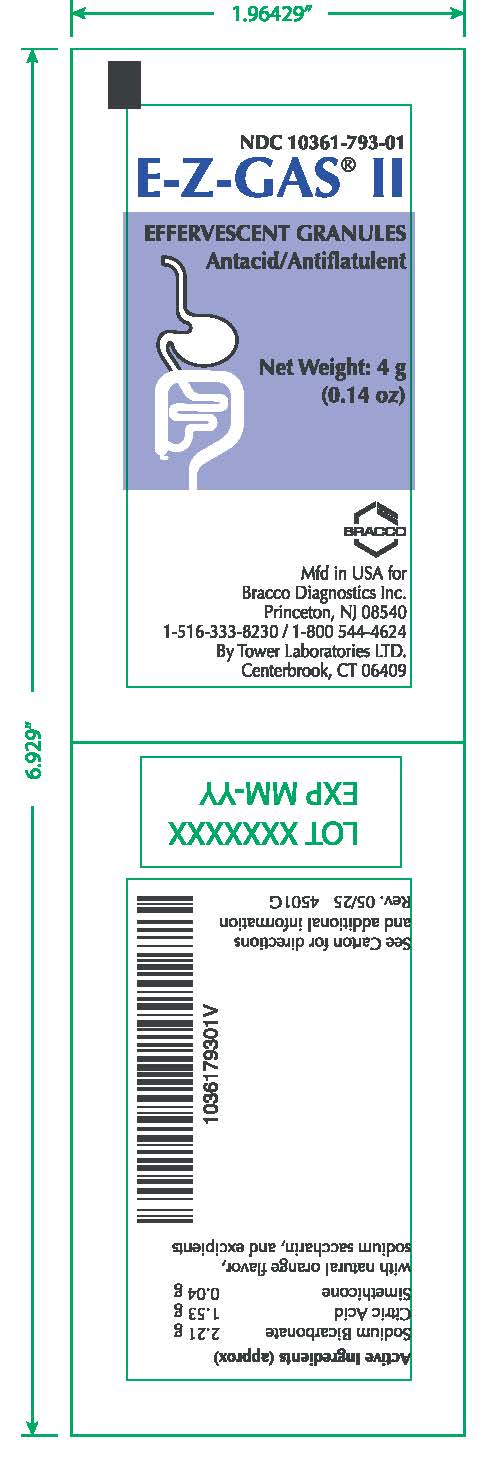 DRUG LABEL: E-Z-GAS
NDC: 10361-793 | Form: GRANULE, EFFERVESCENT
Manufacturer: E-Z-EM, INC.
Category: otc | Type: HUMAN OTC DRUG LABEL
Date: 20251218

ACTIVE INGREDIENTS: ANHYDROUS CITRIC ACID 380 mg/1 g; SODIUM BICARBONATE 550 mg/1 g; DIMETHICONE 10 mg/1 g; SILICON DIOXIDE 10 mg/1 g
INACTIVE INGREDIENTS: Maltodextrin; Saccharin Sodium

E-Z-GAS® II
EFFERVESCENT GRANULES
ANTACID/ANTIFLATULENT

Drug Facts

Active Ingredients (in each packet) | Purpose
Citric Acid 1.53 g | Antacid
Simethicone 0.04 g | Antiflatulent
Sodium Bicarbonate 2.21 g | Antacid

Uses

- relieves
  - heartburn           - acid indigestion
  - sour stomach    - upset stomach
- relieves gas associated with these symptoms

Warnings

Do not use

- In cases of known or suspected esophageal obstruction.
- To dislodge foreign bodies.
- More than the maximum recommended dosage in 24-hour period.
- the maximum dosage of this product for more than two weeks, except under the advice and supervision of a physician.

Ask a doctor before use

- if you are taking a prescription drug. Antacids may interact with certain prescription drugs.
- If you have a sodium restricted diet.

Keep out of reach of children. In case of overdose seek medical help or contact a poison center immediately.

ACTIVE INGREDIENT

Once package is opened, discard unused portion.

Directions

 | Recommended dose | Maximum recommended dose
Adults (under 60 years) | One packet every 6 hours or as directed by physician | Not to exceed 4 packets in 24 hours
Adults (60 years and older) | One packet every 8 hours or as directed by physician | Not to exceed 3 packets in 24 hours
Children (6 to 12 years) | One packet every 8 hours or as directed by physician | Not to exceed 3 packets in 24 hours
Children Under 6 years | Consult physician | Consult physician

Other information

- Store at controlled room temperature 15⁰ - 30⁰ C (59⁰ - 86⁰F).
- Protect from moisture.
- Sodium content: approximately 26 mEq (600 mg) per dose.

Inactive ingredients

Maltodextrin, natural orange flavor, sodium saccharin.

QUESTIONS

Questions? 1-516-333-8230 or 1-800-5444624

PACKAGE LABEL

E-Z-Gas II
NDC: 10361-793-01

E-Z-Gas II Label
NDC: 10361-793-01